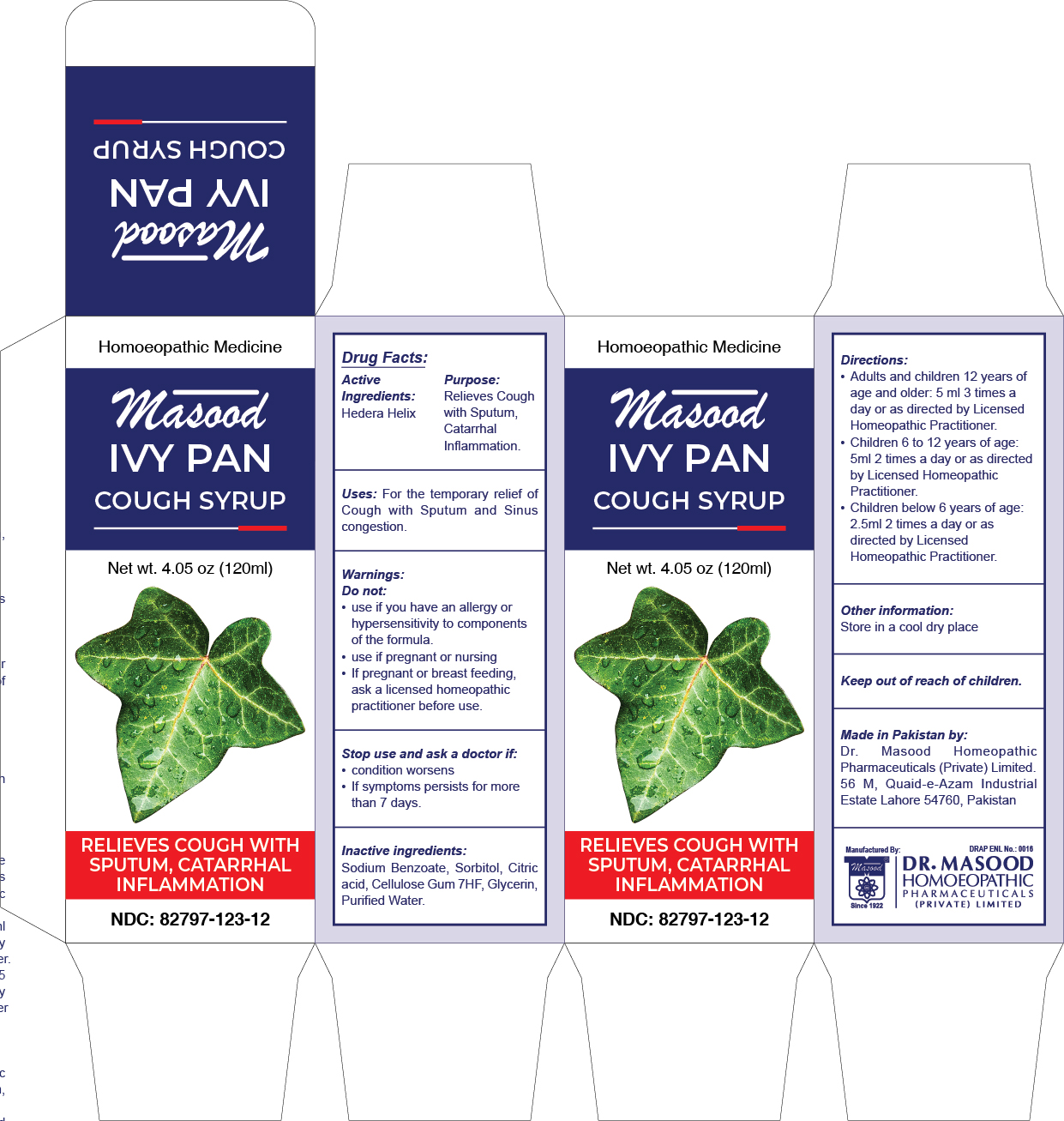 DRUG LABEL: Masood Ivypan Cough Syrup
NDC: 82797-123 | Form: SYRUP
Manufacturer: Dr. Masood Homeopathic Pharmaceuticals Private Limited
Category: homeopathic | Type: HUMAN OTC DRUG LABEL
Date: 20240109

ACTIVE INGREDIENTS: HEDERA HELIX LEAF 9.6 mg/120 mL
INACTIVE INGREDIENTS: SODIUM BENZOATE 0.12 g/120 mL; ANHYDROUS CITRIC ACID 0.18 g/120 mL; GLYCERIN 18 mL/120 mL; WATER 100 mL/120 mL; SORBITOL SOLUTION 70% 0.26 mL/120 mL; CARBOXYMETHYLCELLULOSE SODIUM (0.7 CARBOXYMETHYL SUBSTITUTION PER SACCHARIDE; 100-200 MPA.S AT 1%) 0.5 mg/120 mL

Masood Ivypan Cough Syrup

Directions:

- Adults and children 12 years of age and older: 5 ml 3 times a day or as directed by Licensed Homeopathic Practitioner.
- Children 6 to 12 years of age: 5 ml 2 times a day or as directed by Licensed Homeopathic Practitioner.
- Children below 6 years of age: 2.5 ml 2 times a day or as directed by Licensed Homeopathic Practitioner

Uses:

For the temporary relief of

- Cough with Sputum and Sinus congestion

Warnings:

Do not:

- use if you have an allergy or hypersensitivity to components of the formula
- use if pregnant or nursing

Stop use and ask a doctor if:

- condition worsens
- If symptoms persists for more than 7 days

Active Ingredients

- Hedera Helix

Keep out of reach of children.

Purpose:

- Relieves Cough with Sputum, Catarrhal Inflammation

Inactive Ingredients:

Sodium Benzoate, Sorbitol, Citric acid, Cellulose Gum 7HF, Glycerin, Purified Water